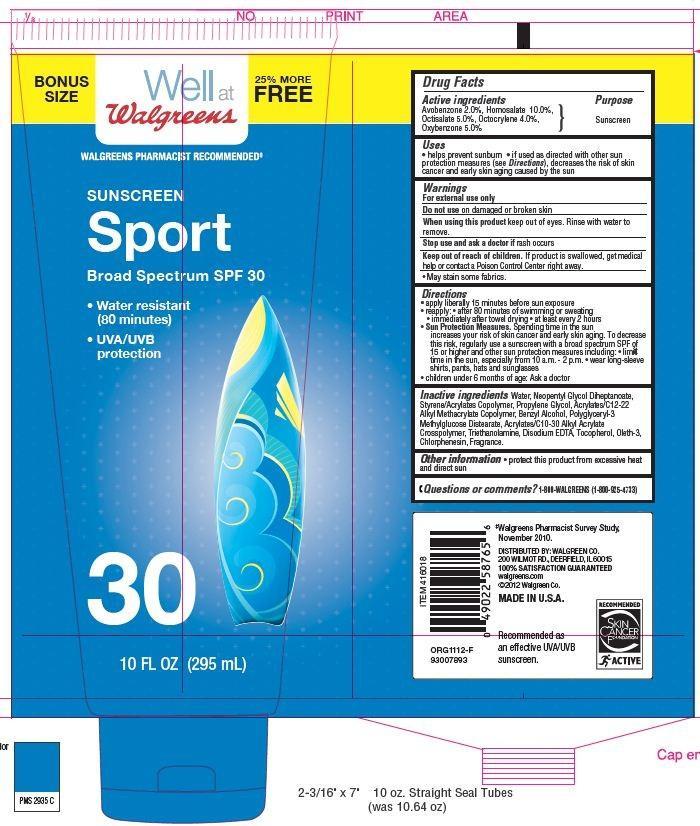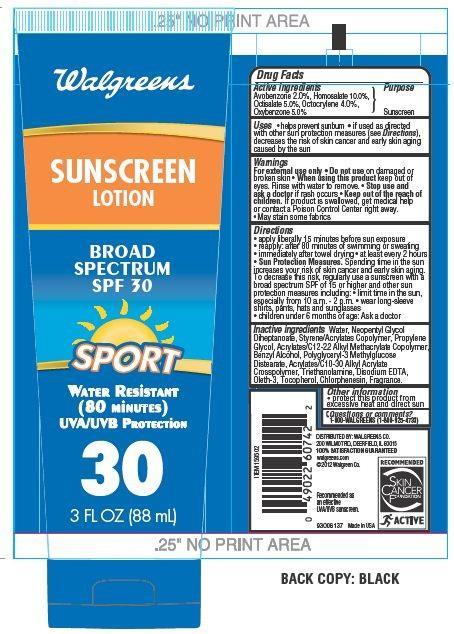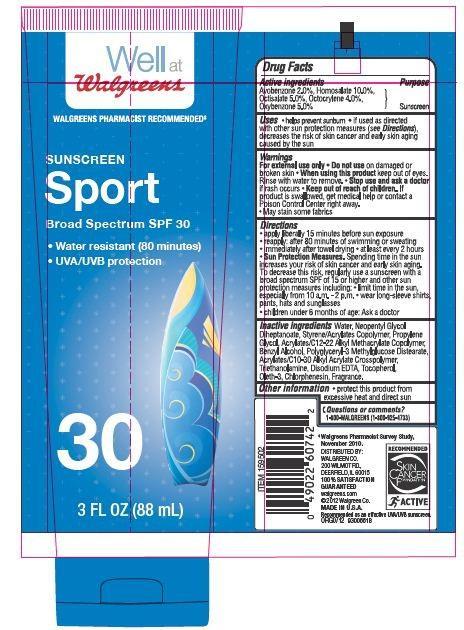 DRUG LABEL: Walgreens SUNSCREEN Sport
NDC: 0363-4015 | Form: LOTION
Manufacturer: WALGREEN CO.
Category: otc | Type: HUMAN OTC DRUG LABEL
Date: 20130807

ACTIVE INGREDIENTS: AVOBENZONE 2 g/100 g; HOMOSALATE 10 g/100 g; OCTISALATE 5 g/100 g; OCTOCRYLENE 4 g/100 g; OXYBENZONE 5 g/100 g
INACTIVE INGREDIENTS: WATER; NEOPENTYL GLYCOL; PROPYLENE GLYCOL; BENZYL ALCOHOL; TROLAMINE; OLETH-3; CHLORPHENESIN; TOCOPHEROL; EDETATE DISODIUM

Drug Facts

Active Ingredients

Avobenzone 2.0 %

Homosalate 10.0%

Octisalate 5.0%

Octocrylene 4.0%

Oxybenzone 5.0%

Purpose

Sunscreen

Uses

- helps prevent sunburn
- if used as directed with other sun protection measures (see Directions) decrease the risk of skin cancer and early skin aging caused by the sun

Warnings

For External use only

Do not use on damaged or broken skin

When using this product

- keep out of eyes. Rinse with water to remove.

stop use and ask a doctor if

rash occurs.

Keep out of reach of children.

If product is swallowed get medical help or contact a Poison Control Center right away.

- May stain some fabrics.

Other Information

protect this product from excessive heat and direct sun

Questions or Comments?: 1-800 WALGREENS (1-800-925-4733)

Directions

- apply liberally 15 minutes before sun exposure
- reapply: after 80 minutes of swimming or sweating
- immediately after towel drying
- at least every 2 hours

Sun protection measures.

Spending time in the sun increase your risk of skin cancer and early skin aging. To decrease this risk regularly use a sunscreen with a broad spectrum SPF of 15 or higher and other sun protection measures including:

- Limit time in the sun, especially from 10 am - 2 pm
- Wear long sleeves shirts, pants, hats and sunglasses
- children under 6 month of age: Ask a doctor

Inactive Ingredients

Water,Neopentyl Glycol, Diheptanoate, Styrene/Acrylates Copolymer, Propylene Glycol, Acrylates/ C12-22 Alkyl Methacrylate Copolymer, Benzyl Alcohol, Polyglyceryl-3 Methylglycose Distearate, Acrylates/C10-30 Alkyl Acrylate Crosspolymer, Triethanolamine, Oleth-3,Chlorphenesin, Tocopherol, Disodium EDTA, Fragrance.

Principal Display Panel

BONUS

SIZE

Well at

Walgreens

25% MORE

FREE

WALGREENS PHARMACY RECOMMENDED

SUNSCREEN

Sport

Broad Spectrum SPF 30

Water resistant

(80 minutes)

UVA/UVB

Protection

10 FL OZ (295 mL)

Walgreens

SUNSCREEN

LOTION

BROAD

SPECTRUM

SPF 30

SPORT

WATER RESISTANT

(80 Minutes)

UVA/UVB Protection

3 FL OZ (88 mL)